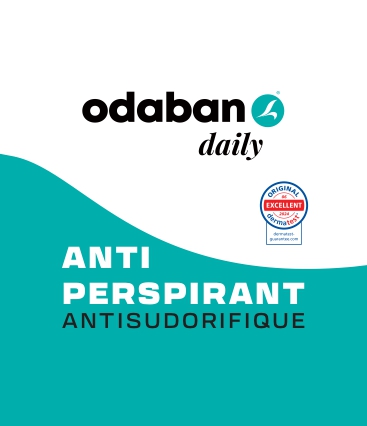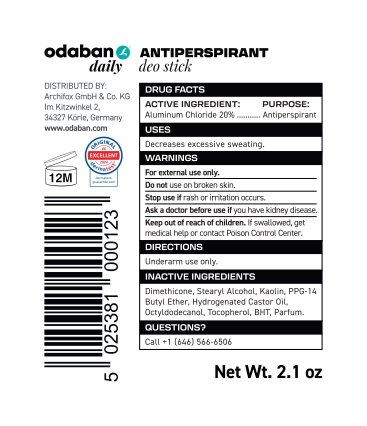 DRUG LABEL: Odaban Antiperspirant Deo Stick
NDC: 84788-0003 | Form: STICK
Manufacturer: Ryma-Pharm GmbH
Category: otc | Type: HUMAN OTC DRUG LABEL
Date: 20260105

ACTIVE INGREDIENTS: ALUMINUM CHLORIDE 12.4 mg/62 mL
INACTIVE INGREDIENTS: TOCOPHEROL; PPG-14 BUTYL ETHER; KAOLIN; DIMETHICONE; HYDROGENATED CASTOR OIL; OCTYLDODECANOL; BHT; STEARYL ALCOHOL

DOSAGE AND ADMINISTRATION

DIRECTIONS Underarm use only.

WARNINGS

Decreases excessive sweating.

INACTIVE INGREDIENT

Dimethicone, Stearyl Alcohol, Kaolin, PPG-14 Butyl Ether, Hydrogenated Castor Oil, Octyldodecanol, Tocopherol, BHT, Parfum.

INDICATIONS AND USAGE

For external use only. Do not use on broken skin. Stop use if rash or irritation occurs. ‘Aska doctor before use if you have kidney disease. Keep out of reach of children. If swallowed, get medical help or contact Poison Control Center.

Keep out of reach of children. If swallowed, get medical help or contact Poison Control Center.

PURPOSE: Antiperspirant

ACTIVE INGREDIENT: Aluminum Chloride 20%

Keep out of reach of children. If swallowed, get medical help or contact Poison Control Center.

PACKAGE LABEL

ANTIPERSPIRANT ANTISUDORIFIQUE

odaban@ daily DISTRIBUTED BY: Archifox GmbH & Co. KG Im Kitzwinkel 2, 34327 Kérle, Germany www.odaban.com 025381 5 ANTIPERSPIRANT deo stick DRUG FACTS ACTIVE INGREDIEN’ PURPOSE: Aluminum Chloride 20%... Antiperspirant re Decreases excessive sweating. WARNINGS For external use only. Do not use on broken skin. Stop use if rash or irritation occurs. ‘Aska doctor before use if you have kidney disease. Keep out of reach of children. If swallowed, get medical help or contact Poison Control Center. DIRECTIONS Underarm use only. reat olan eS) Dimethicone, Stearyl Alcohol, Kaolin, PPG-14 Butyl Ether, Hydrogenated Castor Oil, Octyldodecanol, Tocopherol, BHT, Parfum. QUESTIONS? Net Wt. 2.1 oz